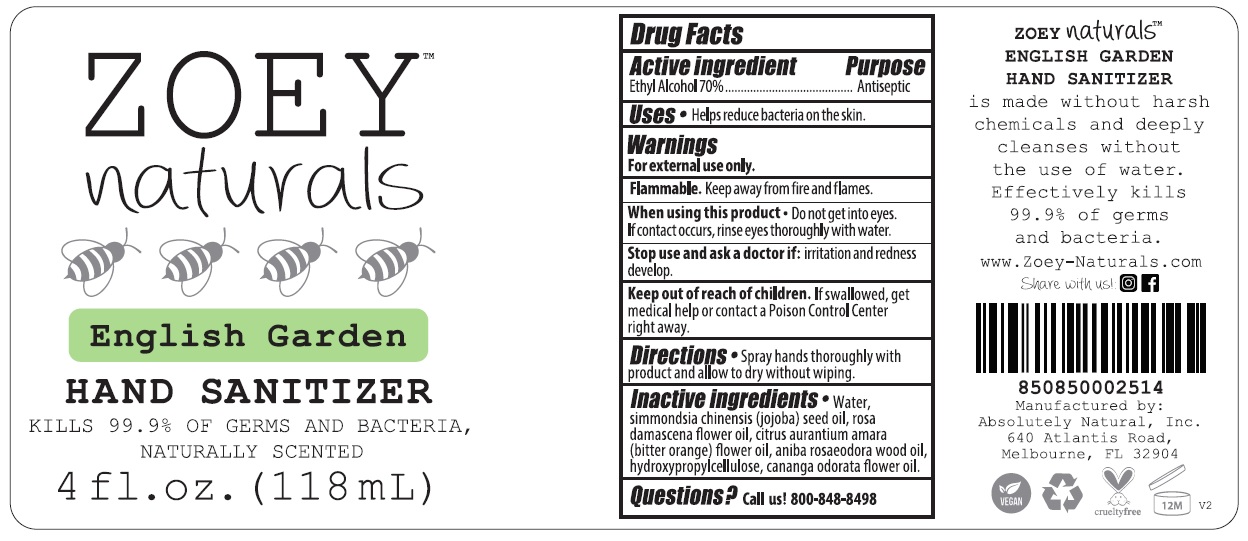 DRUG LABEL: ZOEY naturals English Garden HAND SANITIZER
NDC: 70793-009 | Form: SPRAY
Manufacturer: Absolutely Natural
Category: otc | Type: HUMAN OTC DRUG LABEL
Date: 20241211

ACTIVE INGREDIENTS: ALCOHOL 70 mL/100 mL
INACTIVE INGREDIENTS: WATER; JOJOBA OIL; ROSA X DAMASCENA FLOWER OIL; CITRUS AURANTIUM FLOWER OIL; BRAZILIAN ROSEWOOD OIL; HYDROXYPROPYL CELLULOSE, UNSPECIFIED; YLANG-YLANG OIL

ZOEY™ naturals English Garden HAND SANITIZER

Active ingredient

Ethyl Alcohol 70%

Purpose

Antiseptic

Uses

• Helps reduce bacteria on the skin.

Warnings

For external use only.

Flammable. Keep away from fire and flames.

When using this product • Do not get into eyes. If contact occurs, rinse eyes thoroughly with water.

Stop use and ask a doctor if: irritation and redness develop.

Keep out of reach of children. If swallowed, get medical help or contact a Poison Control Center right away.

Directions

• Spray hands thoroughly with product and allow to dry without wiping.

Inactive ingredients

• Water, simmondsia chinensis (jojoba) seed oil, rosa damascene flower oil, citrus aurantium amara (bitter orange) flower oil, aniba rosaeodora wood oil, hydroxypropylcellulose, cananga odorata flower oil.

Questions?

Call us! 800-848-8498

KILLS 99.9% OF GERMS AND BACTERIA, NATURALLY SCENTED

ZOEY naturals™ ENGLISH GARDEN HAND SANITIZER is made without harsh chemicals and deeply cleanses without the use of water.
Effectively kills 99.9% of germs and bacteria.

www.Zoey-Naturals.com

Share with us!

Manufactured by:

Absolutely Natural, Inc.

640 Atlantis Road,

Melbourne, FL 32904